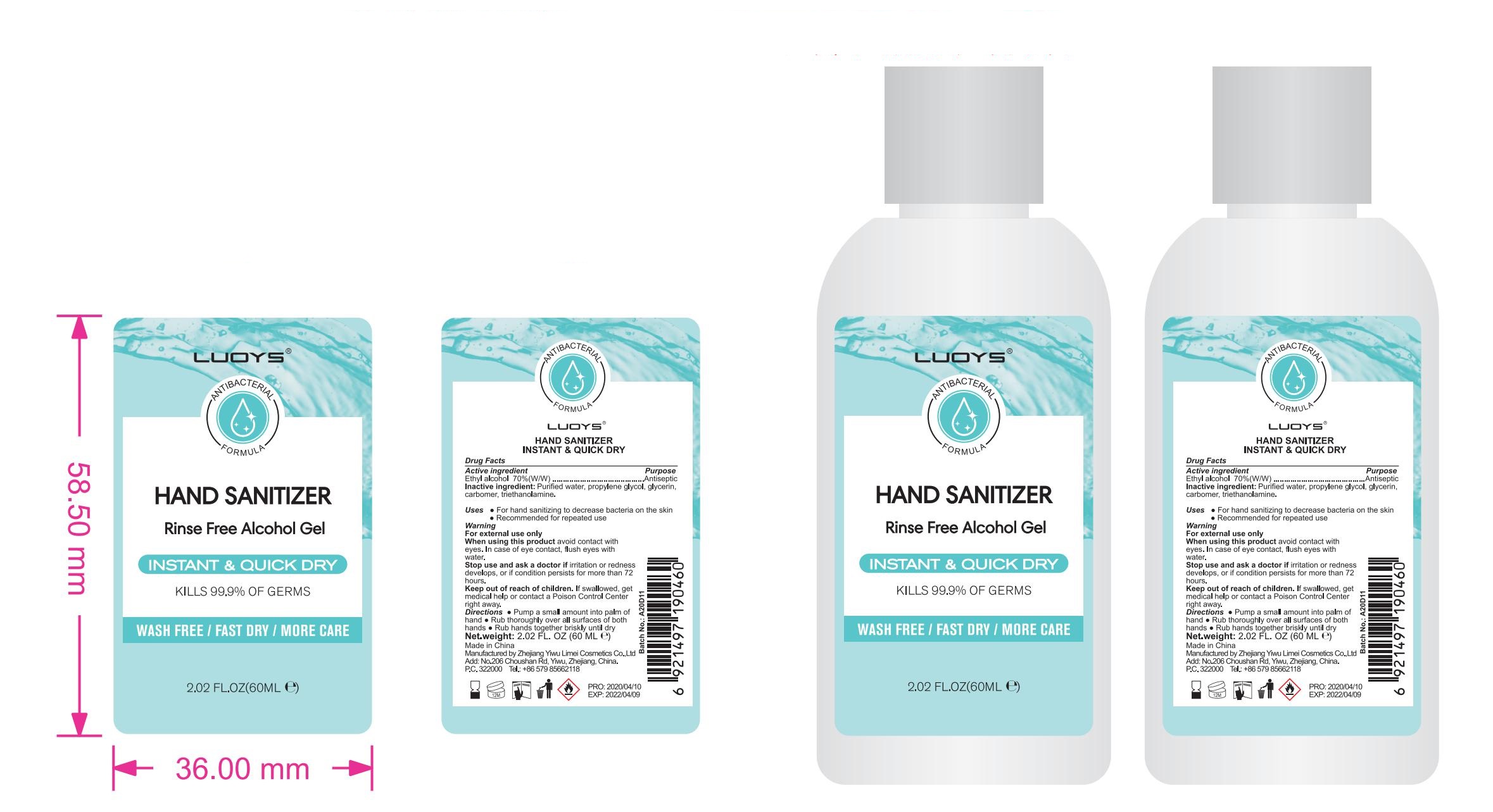 DRUG LABEL: LUOYS Hand Sanitizer
NDC: 74765-005 | Form: GEL
Manufacturer: Zhejiang Yiwu limei Cosmetics Co.,Ltd
Category: otc | Type: HUMAN OTC DRUG LABEL
Date: 20200429

ACTIVE INGREDIENTS: ALCOHOL 70 g/100 g
INACTIVE INGREDIENTS: CARBOMER 980; TROLAMINE; GLYCERIN; PROPYLENE GLYCOL; WATER

NA

Active Ingredient(s)

Ethyl alcohol 70%(w/w) . Purpose: Antiseptic

Purpose

Antiseptic, Hand Sanitizer

Use

For hand sanitizing to decrease bateria on the skin

Recommended for repeated use

Warnings

For external use only.

When using this product keep out of eyes, ears, and mouth. In case of contact with eyes, rinse eyes thoroughly with water.
Stop use and ask a doctor if irritation or rash occurs. These may be signs of a serious condition.
Keep out of reach of children. If swallowed, get medical help or contact a Poison Control Center right away.

Do not use

NA

When using this product keep out of eyes, ears, and mouth. In case of contact with eyes, rinse eyes thoroughly with water.
Stop use and ask a doctor if irritation or rash occurs. These may be signs of a serious condition.
Keep out of reach of children. If swallowed, get medical help or contact a Poison Control Center right away.

Stop use and ask a doctor if irritation or rash occurs. These may be signs of a serious condition.

Keep out of reach of children. If swallowed, get medical help or contact a Poison Control Center right away.

Directions

- Pump a small amount into palm of hand
- Rub thoroughly over all surfaces of both hands.
- Rub hands together briskly until dry

Other information

NA

Inactive ingredients

Purified water, propylene glycol,glycerin, carbomer,triethanolamine

RECENT MAJOR CHANGES

NA

Package Label - Principal Display Panel

60 mL NDC: 74765-005-01

500 mL NDC: 74765-005-02